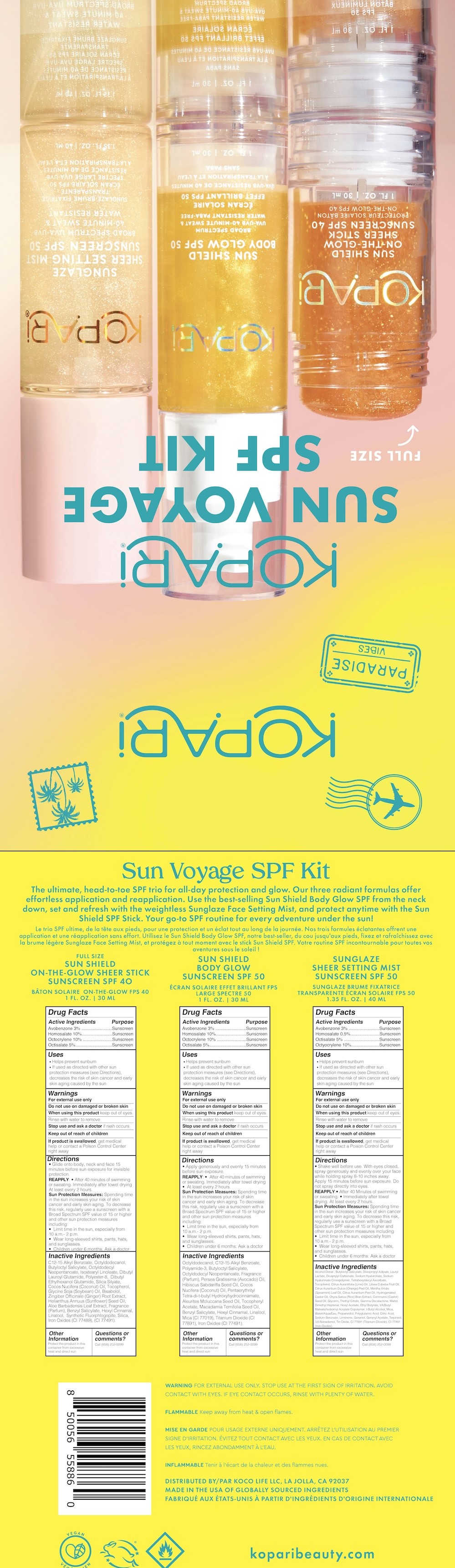 DRUG LABEL: Sun Voyage Kit
NDC: 84130-013 | Form: KIT | Route: TOPICAL
Manufacturer: Koco Life LLC
Category: otc | Type: HUMAN OTC DRUG LABEL
Date: 20241118

ACTIVE INGREDIENTS: OCTOCRYLENE 10 g/100 g; AVOBENZONE 3 g/100 g; OCTISALATE 5 g/100 g; HOMOSALATE 10 g/100 g; AVOBENZONE 30 mg/1 mL; OCTISALATE 50 mg/1 mL; OCTOCRYLENE 100 mg/1 mL; HOMOSALATE 5 mg/1 mL; AVOBENZONE 30 mg/1 mL; OCTISALATE 50 mg/1 mL; OCTOCRYLENE 100 mg/1 mL; HOMOSALATE 100 mg/1 mL
INACTIVE INGREDIENTS: OCTYLDODECYL NEOPENTANOATE; FARNESOL; BENZYL SALICYLATE; LEVOMENOL; ALOE VERA LEAF; ISOSTEARYL LINOLEATE; LINALOOL, (+)-; OCTYLDODECANOL; MAGNESIUM POTASSIUM ALUMINOSILICATE FLUORIDE; COCONUT OIL; DIBUTYL LAUROYL GLUTAMIDE; SUNFLOWER OIL; GINGER; CITRAL; BUTYLOCTYL SALICYLATE; FERRIC OXIDE RED; POLYESTER-8 (1400 MW, CYANODIPHENYLPROPENOYL CAPPED); DIBUTYL ETHYLHEXANOYL GLUTAMIDE; .ALPHA.-HEXYLCINNAMALDEHYDE; SILICON DIOXIDE; SOYBEAN OIL; TOCOPHEROL; ALKYL (C12-15) BENZOATE; GLYCERIN; TERT-BUTYL ALCOHOL; SODIUM BENZOATE; WATER; .GAMMA.-DECALACTONE; HEXYL ACETATE; DIISOPROPYL ADIPATE; RICE BRAN; LIME OIL, COLD PRESSED; TRIETHYL CITRATE; FERRIC OXIDE RED; ALCOHOL; GERANYL ACETATE; LIMONENE, (+)-; STANNOUS OXIDE; SPEARMINT OIL; BITTER ORANGE OIL; TETRAHEXYLDECYL ASCORBATE; HYALURONATE SODIUM; BUTYLOCTYL SALICYLATE; PEG-9 DIGLYCIDYL ETHER/SODIUM HYALURONATE CROSSPOLYMER; DICAPRYLYL CARBONATE; 2,6-DIMETHYL-5-HEPTENAL; CITRIC ACID MONOHYDRATE; PROPANEDIOL; ETHYL BUTYRATE; LITSEA OIL; ORANGE OIL, COLD PRESSED; HYDROGENATED CASTOR OIL; LAURYL LACTATE; TITANIUM DIOXIDE; TOCOPHEROL; MICA; GERANIOL; CASTOR OIL; DIBUTYL MALEATE; TERPINEOL; POLYGLUTAMIC ACID (1200 MW); MALTOL; BUTYLOCTYL SALICYLATE; FERRIC OXIDE RED; OCTYLDODECYL NEOPENTANOATE; OCTYLDODECANOL; POLYAMIDE-3 (12000 MW); AVOCADO OIL; KUKUI NUT OIL; .ALPHA.-TOCOPHEROL ACETATE; MACADAMIA OIL; BENZYL SALICYLATE; PENTAERYTHRITOL TETRAKIS(3-(3,5-DI-TERT-BUTYL-4-HYDROXYPHENYL)PROPIONATE); HIBISCUS SABDARIFFA SEED OIL; LINALOOL, (+/-)-; ALKYL (C12-15) BENZOATE; COCONUT OIL; MICA; .ALPHA.-HEXYLCINNAMALDEHYDE; TITANIUM DIOXIDE

Sun Voyage SPF Kit

84130-004-10 SUN SHIELD ON-THE-GLOW SHEER STICK SPF40

Active Ingredients

Avobenzone 3%

Homosalate 10%

Octocrylene 10%

Octisalate 5%

Purpose

Avobenzone 3% .........................Sunscreen

Homosalate 10%.........................Sunscreen

Octocrylene 10% ........................Sunscreen

Octisalate 5%..............................Sunscreen

Uses

• Helps prevent sunburn

• If used as directed with other sunprotection measures (see Directions),decreases the risk of skin cancer and earlyskin aging caused by the sun

Warnings

For external use only

Do not use on damaged or broken skin

When using this product keep out of eyes.
Rinse with water to remove

Stop use and ask a doctor if rash occurs

Keep out of reach of children
If product is swallowed , get medical help or contact a Poison Control Center right away

Directions

• Glide onto body, neck and face 15 minutes before sun exposure for invisible protection.

REAPPLY: • After 40 minutes of swimming or sweating. Immediately after towel drying At least every 2 hours.

Sun Protection Measures: Spending time in the sun increases your risk of skin cancer and early skin aging. To decrease this risk, regularly use a sunscreen with a Broad Spectrum SPF value of 15 or higher and other sun protection measures including:

• Limit time in the sun, especially from10 a.m.- 2 p.m.

• Wear long-sleeved shirts, pants, hats,and sunglasses.

• Children under 6 months: Ask a doctor

Inactive Ingredients

C12-15 Alkyl Benzoate, Octyldodecanol, Butyloctyl Salicylate, Octyldodecyl Neopentanoate, Isostearyl Linoleate, Dibutyl Lauroyl Glutamide, Polyester-8, Dibutyl Ethylhexanol Glutamide, Silica Silyate, Cocos Nucifera (Coconut) Oil, Tocopherol, Glycine Soja (Soybean) Oil, Bisabolol, Zingiber Officinale (Ginger) Root Extract, Helianthus Annuus (Sunflower) Seed Oil, Aloe Barbadensis Leaf Extract, Fragrance (Parfum), Benzyl Salicylate, Hexyl Cinnamal, Linalool, Synthetic Fluorphlogopite, Silica, Iron Oxides (CI 77489), (CI 77491).

Other Information

Protect the product in this container from excessive heat and direct sun

Questions or comments?

Call (858) 252-0099

84130-001-10 SUN SHIELD BODY GLOW SPF50

Active Ingredients

Avobenzone 3%

Homosalate 10%

Octocrylene 10%

Octisalate 5%

Purpose

Avobenzone 3% .........................Sunscreen

Homosalate 10%.........................Sunscreen

Octocrylene 10% ........................Sunscreen

Octisalate 5%..............................Sunscreen

Uses

• Helps prevent sunburn

• If used as directed with other sunprotection measures (see Directions),decreases the risk of skin cancer and earlyskin aging caused by the sun

Warnings

For external use only

Do not use on damaged or broken skin

When using this product keep out of eyes.
Rinse with water to remove

Stop use and ask a doctor if rash occurs

Keep out of reach of children
If product is swallowed , get medical help or contact a Poison Control Center right away

Directions

• Apply generously and evenly 15 minutes before sun exposure.

REAPPLY: • After 40 minutes of swimming or sweating. Immediately after towel drying • At least every 2 hours.

Sun Protection Measures: Spending time in the sun increases your risk of skin cancer and early skin aging. To decrease this risk, regularly use a sunscreen with a Broad Spectrum SPF value of 15 or higher and other sun protection measures including:

• Limit time in the sun, especially from10 a.m.- 2 p.m.

• Wear long-sleeved shirts, pants, hats,and sunglasses.

• Children under 6 months: Ask a doctor

Inactive Ingredients

Octyldodecanol, C12-15 Alkyl Benzoate, Polyamide-3, Butyloctyl Salicylate, Octyldodecyl Neopentanoate, Fragrance (Parfum), Persea Gratissima (Avocado) Oil, Hibiscus Sabdariffa Seed Oil, Cocos Nucifera (Coconut) Oil, Pentaerythrityl Tetra-di-t-butyl Hydroxyhydrocinnamate, Aleurites Moluccana Seed Oil, Tocopheryl Acetate, Macadamia Ternifolia Seed Oil, Benzyl Salicylate, Hexyl Cinnamal, Linalool, Mica (CI 77019), Titanium Dioxide (CI 77891), Iron Oxides (CI 77491).

Other Information

Protect the product in this container from excessive heat and direct sun

Questions or comments?

Call (858) 252-0099

84130-011-13 SUNGLAZE SHEER SETTING MIST SUNSCREEN SPF50

Active Ingredients

Avobenzone 3%

Homosalate 0.5%

Octisalate 5%

Octyocrylene 10%

Purpose

Avobenzone 3% .........................Sunscreen

Homosalate 0.5%........................Sunscreen

Octisalate 5% .............................Sunscreen

Octyocrylene 10%.......................Sunscreen

Uses

• Helps prevent sunburn

• If used as directed with other sunprotection measures (see Directions),decreases the risk of skin cancer and earlyskin aging caused by the sun

Warnings

For external use only

Do not use on damaged or broken skin

When using this product keep out of eyes.
Rinse with water to remove

Stop use and ask a doctor if rash occurs

Keep out of reach of children
If product is swallowed, get medical help or contact a Poison Control Center right away

Directions

• Shake well before use. With eyes closed, spray generously and evenly over your face while holding spray 8-10 inches away. Apply 15 minutes before sun exposure. Do not spray directly into eyes.

REAPPLY:• After 40 Minutes of swimming or sweating. • Immediately after towel drying. At least every 2 hours.

Sun Protection Measures: Spending time in the sun increases your risk of skin cancer and early skin aging. To decrease this risk, regularly use a sunscreen with a Broad Spectrum SPF value of 15 or higher and other sun protection measures including:

• Limit time in the sun, especially from10 a.m.- 2 p.m.

• Wear long-sleeved shirts, pants, hats,and sunglasses.

• Children under 6 months: Ask a doctor

Inactive Ingredients

Alcohol Denat., Butyloctyl Salicylate, Diisopropyl Adipate, Lauryl Lactate, Dicaprylyl Carbonate, Sodium Hyaluronate, Sodium Hyaluronate Crosspolymer, Tetrahexyldecyl Ascorbate, Tocopherol, Citrus Aurantifolia (Lime) Oil, Litsea Cubeba Fruit Oil, Citrus Aurantium Dulcis (Orange) Peel Oil, Mentha Viridis (Spearmint) Leaf Oil, Citrus Aurantium Peel Oil, Hydrogenated Castor Oil, Oryza Sativa (Rice) Bran Extract, Communis (Castor) Seed Oil, Glycerin, Triethyl Citrate, Gamma Decalactone, Maltol, Dimethyl Heptenal, Hexyl Acetate, Ethyl Butyrate, VA/Butyl Maleate/Isobornyl Acrylate Copolymer, t-Butyl Alcohol, Mica, Water/Aqua/Eau, Propanediol, Polyglutamic Acid, Citric Acid, Sodium Benzoate, Limonene, Geraniol, Geranyl Acetate, Terpineol, 3,6-Nonadienol, Tin Oxide, CI 77891 (Titanium DIoxide), CI 77491 (Iron Oxides)

Other Information

Protect the product in this container from excessive heat and direct sun

Questions or comments?

Call (858) 252-0099

PACKAGE LABEL

Kopari

Sun Voyage

SPF Kit